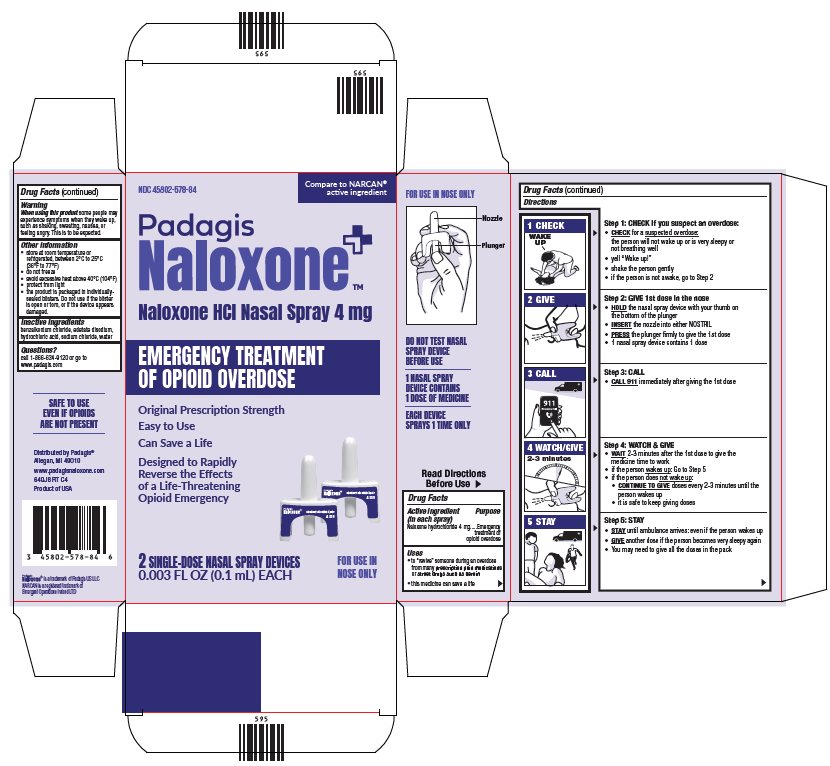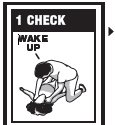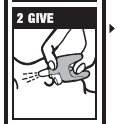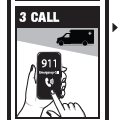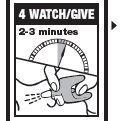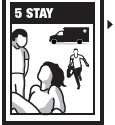 DRUG LABEL: NALOXONE HYDROCHLORIDE
NDC: 45802-578 | Form: SPRAY
Manufacturer: Padagis Israel Pharmaceuticals Ltd
Category: otc | Type: HUMAN OTC DRUG LABEL
Date: 20260106

ACTIVE INGREDIENTS: NALOXONE HYDROCHLORIDE 4 mg/0.1 mL
INACTIVE INGREDIENTS: BENZALKONIUM CHLORIDE; EDETATE DISODIUM; SODIUM CHLORIDE; HYDROCHLORIC ACID; WATER

Naloxone HCl Nasal Spray Drug Facts

Active Ingredient (in each spray)

Naloxone hydrochloride 4 mg

Purpose

Emergency treatment of opioid overdose

Uses

• to “revive” someone during an overdose from many prescription pain medications or street drugs such as heroin

• this medicine can save a life

Directions

EMERGENCY TREATMENT OF OPIOID OVERDOSE

Important:

- For use in the nose only
- Do not test nasal spray device before use
- 1 nasal spray device contains 1 dose of medicine
- Each device sprays 1 time only

Step 1: CHECK if you suspect an overdose:

• CHECK for a suspected overdose: the person will not wake up or is very sleepy or not breathing well

• yell “Wake up!”

• shake the person gently

• if the person is not awake, go to Step 2

Step 2: GIVE 1st dose in the nose

• HOLD the nasal spray device with your thumb on the bottom of the plunger

• INSERT the nozzle into either NOSTRIL

• PRESS the plunger firmly to give the 1st dose

• 1 nasal spray device contains 1 dose

Step 3: CALL

• CALL 911immediately after giving the 1st dose

Step 4: WATCH & GIVE

• WAIT2-3 minutes after the 1st dose to give the medicine time to work

• if the person wakes up: Go to Step 5

• if the person does not wake up:

• CONTINUE TO GIVE doses every 2-3 minutes until the person wakes up

• it is safe to keep giving doses

Step 5: STAY

• STAY until ambulance arrives: even if the person wakes up

• GIVE another dose if the person becomes very sleepy again

• You may need to give all the doses in the pack

For opioid emergencies, call 911. For questions on Naloxone HCl Nasal Spray 4 mg, call Padagis® at 1-866-634-9120 or go to www.padagisnaloxone.com.

Warning

When using this product some people may experience symptoms when they wake up, such as shaking, sweating, nausea, or feeling angry. This is to be expected.

Other information

• store at room temperature or refrigerated, between 2°C to 25°C (36°F to 77°F)

• do not freeze

• avoid excessive heat above 40°C (104°F)

• protect from light

• the product is packaged in individually-sealed blisters. Do not use if the blister is open or torn, or if the device appears damaged.

Inactive Ingredients

benzalkonium chloride, edetate disodium, hydrochloric acid, sodium chloride, water

Questions?

call 1-866-634-9120 or go to www.padagis.com

Package/Label Principal Display Panel

NDC 45802-578-84

Compare to NARCAN® active ingredient

Padagis

Naloxone

Naloxone HCl Nasal Spray 4 mg

Emergency Treatment of Opioid Overdose

Original Prescription Strength

Easy to Use

Can Save a Life

Designed to Rapidly Reverse the Effects of a Life-Threatening Opioid Emergency

2 SINGLE-DOSE NASAL SPRAY DEVICES

0.003 FL OZ (0.1mL) EACH

FOR USE IN NOSE ONLY

DO NOT TEST NASAL SPRAY DEVICE BEFORE USE

1 NASAL SPRAY DEVICE CONTAINS 1 DOSE OF MEDICINE

EACH DEVICE SPRAYS 1 TIME ONLY

SAFE TO USE EVEN IF OPIOIDS ARE NOT PRESENT

Distributed by Padagis®
Allegan, MI 49010

www.padagisnaloxone.com

64QJ8 RT C4

Product of USA

64Q00 RT QS5